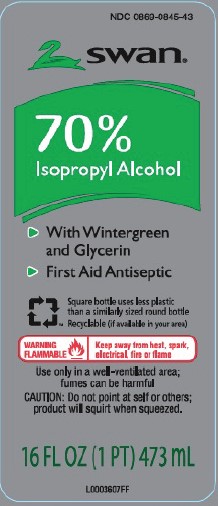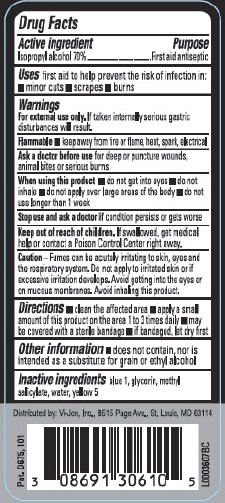 DRUG LABEL: 70% Rubbing
NDC: 0869-0845 | Form: LIQUID
Manufacturer: Vi-Jon, LLC
Category: otc | Type: HUMAN OTC DRUG LABEL
Date: 20250701

ACTIVE INGREDIENTS: ISOPROPYL ALCOHOL 70 mL/100 mL
INACTIVE INGREDIENTS: FD&C BLUE NO. 1; GLYCERIN; METHYL SALICYLATE; WATER; FD&C YELLOW NO. 5

Swan 845.003/845AE
70% IPA, Wintergreen

Active ingredient

Isopropyl alcohol 70%

Purpose

First aid antiseptic

Uses

first aid to help prevent the risk of infection in:

- minor cuts
- scarapes
- burns

Warnings

For external use only.If taken internally serious gastric disturbances will result.

Flammable

keep away from fire or flame, heat, spark, electrical

Ask a doctor before use

for deep or puncture wounds, animal bites or serious burns

When using this product

- do not get into eyes
- do not inhale
- do not apply over large areas of the body
- do not use longer than 1 week

Stop use and ask a doctor if

condition persists or gets worse

Keep out of reach of children.

If swallowed, get medical help or contact a Poison Control Center right away.

Caution

Fumes can be acutuely irritating to skin, eyes and the respiratory system. Do not apply to irritated skin or if excessive irritation develops. Avoid getting into the eyes or on mucous membranes. Avoid inhaling this product.

Directions

- clean the affected area
- apply a small amount of the is product on the affected area 1 to 3 times daily
- may be covered with a sterile bandage
- if bandaged, let dry first

Other Information

- does not contain, nor is intended as a substitute for grain or ethyl alcohol

Inactive ingredient

blue 1, glycerin, methyl salicylate, water, yellow 5

Adverse reaction

Distributed by: Vi-Jon, LLC

One Swan Drive, Smyrna, TN 37167

Pat. D675, 101

principal display panel

NDC 0869-0845-43

swan®

70% Isopropyl Alcohol

- With Wintergreen and Glycerin
- First Aid Antiseptic

Square bottle uses less plastic than a similarly sized round bottle

Recyclable (if available in your area)

WARNING FLAMMALBE - Keep away from heat, spark, electrical, fire or flame

Use only in a well-ventilated area; fumes can be harmful

CAUTION: Do not point at self or others; product will squirt when squeezed.

16 FL OZ (1 PT) 473 mL